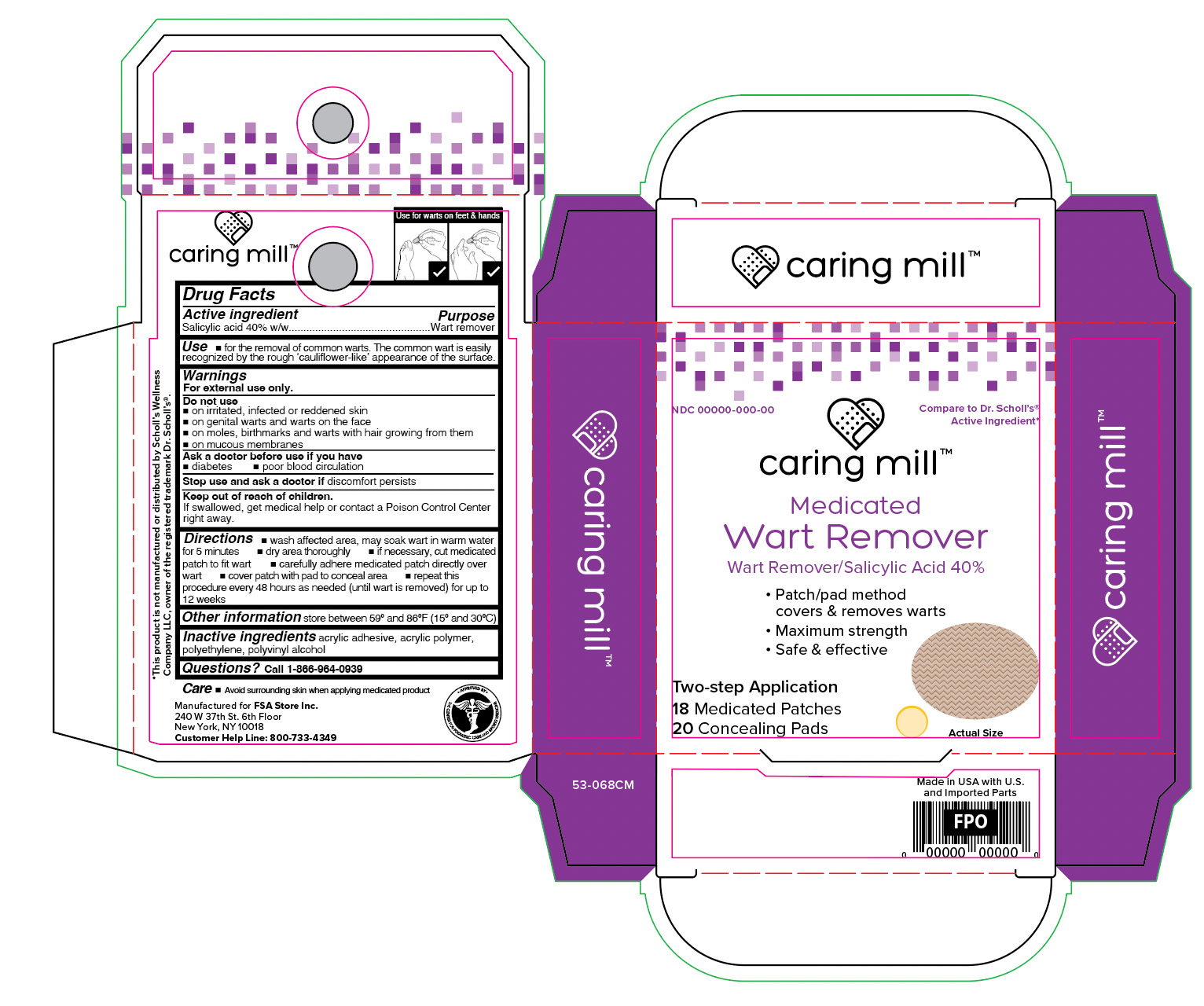 DRUG LABEL: Wart Removers
NDC: 81522-076 | Form: PATCH
Manufacturer: FSA Store Inc.
Category: otc | Type: HUMAN OTC DRUG LABEL
Date: 20241107

ACTIVE INGREDIENTS: SALICYLIC ACID 0.4 g/1 g
INACTIVE INGREDIENTS: POLYVINYL ALCOHOL; VINYL ACETATE; HIGH DENSITY POLYETHYLENE

Caring Mills Wart Removers

Active ingredient

Salicylic acid

Purpose

Wart remover

Use

for the removal of common warts. The common wart is easily recognized by the rough 'cauliflower-like' appearance of the surface.

Warnings

For external use only.

Ask a doctor before use if you have

- diabetes
- poor blood circulation

Do not use on

- irritated, infected or reddened skin
- genital warts and warts on face
- moles, birthmarks and warts with hair growing from them
- mucous membranes

Keep out of reach of children

If swallowed, get medical help or contact a Poison Control Center right away.

Stop and ask a doctor

If discomfort persists

Directions

- wash affected area, may soak wart in warm water for 5 minutes
- dry area thoroughly
- if necessary, cut medicated patch to fit wart
- apply adhesive side down of patch onto wartcover patch with pad to conceal area
- repeat this procedure every 48 hours as needed (until wart is removed) for up to 12 weeks

Other information

store between 59°F to 86°F (15°C to 30°C)

Inactive ingredients

acrylic adhesive, acrylic polymer, polyethylene, polyvinyl alcohol.

Questions?

call 1-866-964-0939

Principal Display Panel

Caring Mill

Medicated

Wart Remover

Wart Remover/Salycylic Acid 40%

- Patch/Pad method covers and removes wart
- Maximum Strength
- Safe & effective

Two Step Application

18 Medicated Patches/20 Concealing Pads